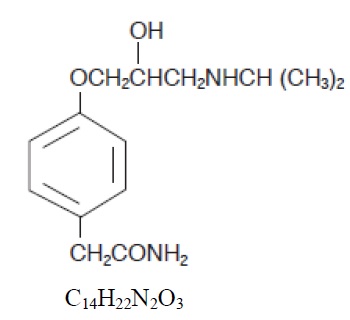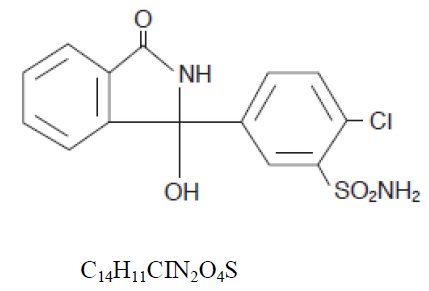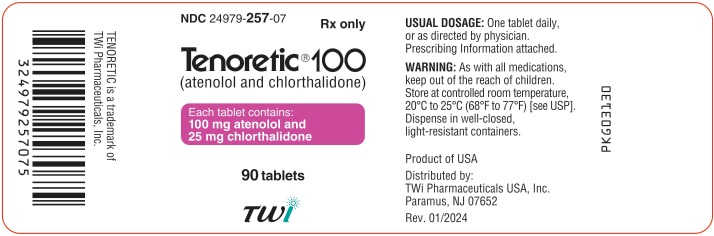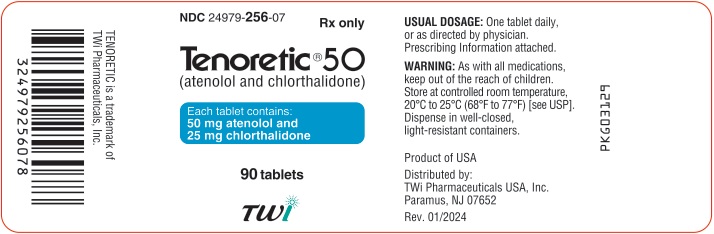 DRUG LABEL: TENORETIC
NDC: 24979-257 | Form: TABLET
Manufacturer: Upsher-Smith Laboratories, LLC
Category: prescription | Type: HUMAN PRESCRIPTION DRUG LABEL
Date: 20240805

ACTIVE INGREDIENTS: ATENOLOL 100 mg/1 1; CHLORTHALIDONE 25 mg/1 1
INACTIVE INGREDIENTS: MAGNESIUM STEARATE; MICROCRYSTALLINE CELLULOSE; POVIDONE, UNSPECIFIED; SODIUM STARCH GLYCOLATE TYPE A POTATO

TENORETIC®
(atenolol and chlorthalidone) Tablets

DESCRIPTION

TENORETIC® (atenolol and chlorthalidone) is for the treatment of hypertension. It combines the antihypertensive activity of two agents: a beta1-selective (cardioselective) hydrophilic blocking agent (atenolol, TENORMIN®) and a monosulfonamyl diuretic (chlorthalidone). Atenolol is Benzeneacetamide, 4-[2'-hydroxy-3'-[(1-methylethyl) amino] propoxy]-.

Atenolol (free base) is a relatively polar hydrophilic compound with a water solubility of 26.5 mg/mL at 37°C. It is freely soluble in 1N HCl (300 mg/mL at 25°C) and less soluble in chloroform (3 mg/mL at 25°C).

Chlorthalidone is 2-Chloro-5-(1-hydroxy-3-oxo-1-isoindolinyl) benzene sulfonamide:

Chlorthalidone has a water solubility of 12 mg/100 mL at 20°C.

Each TENORETIC 100 Tablet contains:

Atenolol (TENORMIN®).......................................100 mg

Chlorthalidone........................................................ 25 mg

Each TENORETIC 50 Tablet contains:

Atenolol (TENORMIN®).........................................50 mg

Chlorthalidone..........................................................25 mg

Inactive ingredients: magnesium stearate, microcrystalline cellulose, povidone, sodium starch glycolate.

CLINICAL PHARMACOLOGY

Tenoretic

Atenolol and chlorthalidone have been used singly and concomitantly for the treatment of hypertension. The antihypertensive effects of these agents are additive, and studies have shown that there is no interference with bioavailability when these agents are given together in the single combination tablet. Therefore, this combination provides a convenient formulation for the concomitant administration of these two entities. In patients with more severe hypertension, TENORETIC may be administered with other antihypertensives such as vasodilators.

Atenolol

Atenolol is a beta1-selective (cardioselective) beta-adrenergic receptor blocking agent without membrane stabilizing or intrinsic sympathomimetic (partial agonist) activities. This preferential effect is not absolute, however, and at higher doses, atenolol inhibits beta2-adrenoreceptors, chiefly located in the bronchial and vascular musculature.

Pharmacodynamics

In standard animal or human pharmacological tests, beta-adrenoreceptor blocking activity of atenolol has been demonstrated by: (1) reduction in resting and exercise heart rates and cardiac output, (2) reduction of systolic and diastolic blood pressure at rest and on exercise, (3) inhibition of isoproterenol induced tachycardia and (4) reduction in reflex orthostatic tachycardia.

A significant beta-blocking effect of atenolol, as measured by reduction of exercise tachycardia, is apparent within one hour following oral administration of a single dose. This effect is maximal at about 2 to 4 hours and persists for at least 24 hours. The effect at 24 hours is dose related and also bears a linear relationship to the logarithm of plasma atenolol concentration. However, as has been shown for all beta-blocking agents, the antihypertensive effect does not appear to be related to plasma level.

In normal subjects, the beta1-selectivity of atenolol has been shown by its reduced ability to reverse the beta2-mediated vasodilating effect of isoproterenol as compared to equivalent beta-blocking doses of propranolol. In asthmatic patients, a dose of atenolol producing a greater effect on resting heart rate than propranolol resulted in much less increase in airway resistance. In a placebo controlled comparison of approximately equipotent oral doses of several beta-blockers, atenolol produced a significantly smaller decrease of FEV1 than nonselective beta-blockers, such as propranolol and unlike those agents did not inhibit bronchodilation in response to isoproterenol.

Consistent with its negative chronotropic effect due to beta blockade of the SA node, atenolol increases sinus cycle length and sinus node recovery time. Conduction in the AV node is also prolonged. Atenolol is devoid of membrane stabilizing activity, and increasing the dose well beyond that producing beta blockade does not further depress myocardial contractility. Several studies have demonstrated a moderate (approximately 10%) increase in stroke volume at rest and exercise.

In controlled clinical trials, atenolol given as a single daily dose, was an effective antihypertensive agent providing 24-hour reduction of blood pressure. Atenolol has been studied in combination with thiazide-type diuretics and the blood pressure effects of the combination are approximately additive. Atenolol is also compatible with methyldopa, hydralazine and prazosin, the combination resulting in a larger fall in blood pressure than with the single agents. The dose range of atenolol is narrow, and increasing the dose beyond 100 mg once daily is not associated with increased antihypertensive effect. The mechanisms of the antihypertensive effects of beta-blocking agents have not been established. Several mechanisms have been proposed and include: (1) competitive antagonism of catecholamines at peripheral (especially cardiac) adrenergic neuron sites, leading to decreased cardiac output, (2) a central effect leading to reduced sympathetic outflow to the periphery and (3) suppression of renin activity. The results from long-term studies have not shown any diminution of the antihypertensive efficacy of atenolol with prolonged use.

Pharmacokinetics and Metabolism

In man, absorption of an oral dose is rapid and consistent but incomplete. Approximately 50% of an oral dose is absorbed from the gastrointestinal tract, the remainder being excreted unchanged in the feces. Peak blood levels are reached between 2 and 4 hours after ingestion. Unlike propranolol or metoprolol, but like nadolol, hydrophilic atenolol undergoes little or no metabolism by the liver, and the absorbed portion is eliminated primarily by renal excretion. Atenolol also differs from propranolol in that only a small amount (6% to 16%) is bound to proteins in the plasma. This kinetic profile results in relatively consistent plasma drug levels with about a fourfold interpatient variation. There is no information as to the pharmacokinetic effect of atenolol on chlorthalidone.

The elimination half-life of atenolol is approximately 6 to 7 hours and there is no alteration of the kinetic profile of the drug by chronic administration. Following doses of 50 mg or 100 mg, both beta-blocking and antihypertensive effects persist for at least 24 hours. When renal function is impaired, elimination of atenolol is closely related to the glomerular filtration rate; but significant accumulation does not occur until the creatinine clearance falls below 35 mL/min/1.73m^2 (see prescribing information for atenolol [TENORMIN®]).

Atenolol Geriatric Pharmacology

In general, elderly patients present higher atenolol plasma levels with total clearance values about 50% lower than younger subjects. The half-life is markedly longer in the elderly compared to younger subjects. The reduction of atenolol clearance follows the general trend that the elimination of renally excreted drugs is decreased with increasing age.

Chlorthalidone:

Chlorthalidone is a monosulfonamyl diuretic which differs chemically from thiazide diuretics in that a double ring system is incorporated in its structure. It is an oral diuretic with prolonged action and low toxicity. The diuretic effect of the drug occurs within 2 hours of an oral dose. It produces diuresis with greatly increased excretion of sodium and chloride. At maximal therapeutic dosage, chlorthalidone is approximately equal in its diuretic effect to comparable maximal therapeutic doses of benzothiadiazine diuretics. The site of action appears to be the cortical diluting segment of the ascending limb of Henle's loop of the nephron.

INDICATIONS AND USAGE

TENORETIC is indicated for the treatment of hypertension, to lower blood pressure. Lowering blood pressure lowers the risk of fatal and non-fatal cardiovascular events, primarily strokes and myocardial infarctions. These benefits have been seen in controlled trials of antihypertensive drugs from a wide variety of pharmacologic classes including atenolol and chlorthalidone.

Control of high blood pressure should be part of comprehensive cardiovascular risk management, including, as appropriate, lipid control, diabetes management, antithrombotic therapy, smoking cessation, exercise, and limited sodium intake. Many patients will require more than 1 drug to achieve blood pressure goals. For specific advice on goals and management, see published guidelines, such as those of the National High Blood Pressure Education Program’s Joint National Committee on Prevention, Detection, Evaluation, and Treatment of High Blood Pressure (JNC).

Numerous antihypertensive drugs, from a variety of pharmacologic classes and with different mechanisms of action, have been shown in randomized controlled trials to reduce cardiovascular morbidity and mortality, and it can be concluded that it is blood pressure reduction, and not some other pharmacologic property of the drugs, that is largely responsible for those benefits. The largest and most consistent cardiovascular outcome benefit has been a reduction in the risk of stroke, but reductions in myocardial infarction and cardiovascular mortality also have been seen regularly.

Elevated systolic or diastolic pressure causes increased cardiovascular risk, and the absolute risk increase per mmHg is greater at higher blood pressures, so that even modest reductions of severe hypertension can provide substantial benefit. Relative risk reduction from blood pressure reduction is similar across populations with varying absolute risk, so the absolute benefit is greater in patients who are at higher risk independent of their hypertension (for example, patients with diabetes or hyperlipidemia), and such patients would be expected to benefit from more aggressive treatment to a lower blood pressure goal.

Some antihypertensive drugs have smaller blood pressure effects (as monotherapy) in black patients, and many antihypertensive drugs have additional approved indications and effects (e.g., on angina, heart failure, or diabetic kidney disease). These considerations may guide selection of therapy.

This fixed dose combination drug is not indicated for initial therapy of hypertension. If the fixed dose combination represents the dose appropriate to the individual patient's needs, it may be more convenient than the separate components.

CONTRAINDICATIONS

TENORETIC is contraindicated in patients with: sinus bradycardia; heart block greater than first degree; cardiogenic shock; overt cardiac failure (see WARNINGS); anuria; hypersensitivity to this product or to sulfonamide-derived drugs.

WARNINGS

Cardiac Failure

Sympathetic stimulation is necessary in supporting circulatory function in congestive heart failure, and beta blockade carries the potential hazard of further depressing myocardial contractility and precipitating more severe failure.

IN PATIENTS WITHOUT A HISTORY OF CARDIAC FAILURE, continued depression of the myocardium with beta-blocking agents over a period of time can, in some cases, lead to cardiac failure. At the first sign or symptom of impending cardiac failure, patients should be treated appropriately according to currently recommended guidelines, and the response observed closely. If cardiac failure continues despite adequate treatment, TENORETIC should be withdrawn. (See DOSAGE AND ADMINISTRATION.)

Renal and Hepatic Disease and Electrolyte Disturbances

Since atenolol is excreted via the kidneys, TENORETIC should be used with caution in patients with impaired renal function.

In patients with renal disease, thiazides may precipitate azotemia. Since cumulative effects may develop in the presence of impaired renal function, if progressive renal impairment becomes evident, TENORETIC should be discontinued.

In patients with impaired hepatic function or progressive liver disease, minor alterations in fluid and electrolyte balance may precipitate hepatic coma. TENORETIC should be used with caution in these patients.

Ischemic Heart Disease

Following abrupt cessation of therapy with certain beta-blocking agents in patients with coronary artery disease, exacerbations of angina pectoris and, in some cases, myocardial infarction have been reported. Therefore, such patients should be cautioned against interruption of therapy without the physician's advice. Even in the absence of overt angina pectoris, when discontinuation of TENORETIC is planned, the patient should be carefully observed and should be advised to limit physical activity to a minimum. TENORETIC should be reinstated if withdrawal symptoms occur. Because coronary artery disease is common and may be unrecognized, it may be prudent not to discontinue TENORETIC therapy abruptly even in patients treated only for hypertension.

Concomitant Use of Calcium Channel Blockers

Bradycardia and heart block can occur and the left ventricular end diastolic pressure can rise when beta-blockers are administered with verapamil or diltiazem. Patients with pre-existing conduction abnormalities or left ventricular dysfunction are particularly susceptible. (See PRECAUTIONS.)

Bronchospastic Diseases

PATIENTS WITH BRONCHOSPASTIC DISEASE SHOULD, IN GENERAL, NOT RECEIVE BETA-BLOCKERS. Because of its relative beta1-selectivity, however, TENORETIC may be used with caution in patients with bronchospastic disease who do not respond to or cannot tolerate, other antihypertensive treatment. Since beta1-selectivity is not absolute, the lowest possible dose of TENORETIC should be used and a beta2-stimulating agent (bronchodilator) should be made available. If dosage must be increased, dividing the dose should be considered in order to achieve lower peak blood levels.

Major Surgery

Chronically administered beta-blocking therapy should not be routinely withdrawn prior to major surgery, however the impaired ability of the heart to respond to reflex adrenergic stimuli may augment the risks of general anesthesia and surgical procedures.

Metabolic and Endocrine Effects

Beta-blockers may prevent early warning signs of hypoglycemia, such as tachycardia, and increase the risk for severe or prolonged hypoglycemia at any time during treatment, especially in patients with diabetes mellitus or children and patients who are fasting (i.e., surgery, not eating regularly, or are vomiting). If severe hypoglycemia occurs, patients should be instructed to seek emergency treatment.

Insulin requirements in diabetic patients may be increased, decreased or unchanged; latent diabetes mellitus may become manifest during chlorthalidone administration.

Beta-adrenergic blockade may mask certain clinical signs (e.g., tachycardia) of hyperthyroidism. Abrupt withdrawal of beta blockade might precipitate a thyroid storm; therefore, patients suspected of developing thyrotoxicosis from whom TENORETIC therapy is to be withdrawn should be monitored closely.

Because calcium excretion is decreased by thiazides, TENORETIC should be discontinued before carrying out tests for parathyroid function. Pathologic changes in the parathyroid glands, with hypercalcemia and hypophosphatemia, have been observed in a few patients on prolonged thiazide therapy; however, the common complications of hyperparathyroidism such as renal lithiasis, bone resorption, and peptic ulceration have not been seen.

Hyperuricemia may occur, or acute gout may be precipitated in certain patients receiving thiazide therapy.

Untreated Pheochromocytoma

TENORETIC should not be given to patients with untreated pheochromocytoma.

Pregnancy and Fetal Injury

Atenolol can cause fetal harm when administered to a pregnant woman. Atenolol crosses the placental barrier and appears in cord blood. Administration of atenolol, starting in the second trimester of pregnancy, has been associated with the birth of infants that are small for gestational age. No studies have been performed on the use of atenolol in the first trimester and the possibility of fetal injury cannot be excluded. If this drug is used during pregnancy, or if the patient becomes pregnant while taking this drug, the patient should be apprised of the potential hazard to the fetus.

Neonates born to mothers who are receiving atenolol at parturition or breastfeeding may be at risk for hypoglycemia and bradycardia. Caution should be exercised when TENORETIC is administered during pregnancy or to a woman who is breastfeeding. (See PRECAUTIONS, Nursing Mothers.)

TENORETIC was studied for teratogenic potential in the rat and rabbit. Doses of atenolol/chlorthalidone of 8/2 mg/kg/day, 80/20 mg/kg/day, and 240/60 mg/kg/day were administered orally to pregnant rats with no evidence of embryofetotoxicity observed. Two studies were conducted in rabbits. In the first study, pregnant rabbits were dosed with 8/2 mg/kg/day, 80/20 mg/kg/day, and 160/40 mg/kg/day of atenolol/chlorthalidone. No teratogenic effects were noted, but embryonic resorptions were observed at all dose levels (ranging from approximately 5 times to 100 times the maximum recommended human dose*). In the second rabbit study, doses of atenolol/chlorthalidone were 4/1 mg/kg/day, 8/2 mg/kg/day, and 20/5 mg/kg/day. No teratogenic or embryotoxic effects were demonstrated.

Atenolol

Atenolol has been shown to produce a dose-related increase in embryo/fetal resorptions in rats at doses equal to or greater than 50 mg/kg/day or 25 or more times the maximum recommended human antihypertensive dose.* Although similar effects were not seen in rabbits, the compound was not evaluated in rabbits at doses above 25 mg/kg/day or 12.5 times the maximum recommended human antihypertensive dose.*

Chlorthalidone

Thiazides cross the placental barrier and appear in cord blood. The use of chlorthalidone and related drugs in pregnant women requires that the anticipated benefits of the drug be weighed against possible hazards to the fetus. These hazards include fetal or neonatal jaundice, thrombocytopenia and possibly other adverse reactions which have occurred in the adult.

*Based on the maximum dose of 100 mg/day in a 50 kg patient.

PRECAUTIONS

General

TENORETIC may aggravate peripheral arterial circulatory disorders.

Information for Patients

Hypoglycemia

Inform patients or caregivers that there is a risk of hypoglycemia when TENORETIC is given to patients who are fasting or who are vomiting. Monitor for symptoms of hypoglycemia.

Electrolyte and Fluid Balance Status

Periodic determination of serum electrolytes to detect possible electrolyte imbalance should be performed at appropriate intervals.

Patients should be observed for clinical signs of fluid or electrolyte imbalance; i.e., hyponatremia, hypochloremic alkalosis, and hypokalemia. Serum and urine electrolyte determinations are particularly important when the patient is vomiting excessively or receiving parenteral fluids. Warning signs or symptoms of fluid and electrolyte imbalance include dryness of the mouth, thirst, weakness, lethargy, drowsiness, restlessness, muscle pains or cramps, muscular fatigue, hypotension, oliguria, tachycardia, and gastrointestinal disturbances such as nausea and vomiting.

Measurement of potassium levels is appropriate especially in elderly patients, those receiving digitalis preparations for cardiac failure, patients whose dietary intake of potassium is abnormally low, or those suffering from gastrointestinal complaints.

Hypokalemia may develop especially with brisk diuresis, when severe cirrhosis is present, or during concomitant use of corticosteroids or ACTH.

Interference with adequate oral electrolyte intake will also contribute to hypokalemia. Hypokalemia can sensitize or exaggerate the response of the heart to the toxic effects of digitalis (e.g., increased ventricular irritability). Hypokalemia may be avoided or treated by use of potassium supplements or foods with a high potassium content.

Any chloride deficit during thiazide therapy is generally mild and usually does not require specific treatment except under extraordinary circumstances (as in liver disease or renal disease). Dilutional hyponatremia may occur in edematous patients in hot weather; appropriate therapy is water restriction rather than administration of salt except in rare instances when the hyponatremia is life-threatening. In actual salt depletion, appropriate replacement is the therapy of choice.

Drug Interactions

TENORETIC may potentiate the action of other antihypertensive agents used concomitantly. Patients treated with TENORETIC plus a catecholamine depletor (e.g., reserpine) should be closely observed for evidence of hypotension and/or marked bradycardia which may produce vertigo, syncope or postural hypotension.

Calcium channel blockers may also have an additive effect when given with TENORETIC. (See WARNINGS.)

Disopyramide is a Type I antiarrhythmic drug with potent negative inotropic and chronotropic effects. Disopyramide has been associated with severe bradycardia, asystole and heart failure when administered with beta-blockers.

Amiodarone is an antiarrhythmic agent with negative chronotropic properties that may be additive to those seen with beta-blockers.

Thiazides may decrease arterial responsiveness to norepinephrine. This diminution is not sufficient to preclude the therapeutic effectiveness of norepinephrine. Thiazides may increase the responsiveness to tubocurarine.

Concomitant use of prostaglandin synthase inhibiting drugs, e.g., indomethacin, may decrease the hypotensive effects of beta-blockers.

Lithium generally should not be given with diuretics because they reduce its renal clearance and add a high risk of lithium toxicity. Read prescribing information for lithium preparations before use of such preparations with TENORETIC.

Beta-blockers may exacerbate the rebound hypertension which can follow the withdrawal of clonidine. If the two drugs are coadministered, the beta-blocker should be withdrawn several days before the gradual withdrawal of clonidine. If replacing clonidine by beta-blocker therapy, the introduction of beta-blockers should be delayed for several days after clonidine administration has stopped.

While taking beta-blockers, patients with a history of anaphylactic reaction to a variety of allergens may have a more severe reaction on repeated challenge, either accidental, diagnostic or therapeutic. Such patients may be unresponsive to the usual doses of epinephrine used to treat the allergic reaction.

Both digitalis glycosides and beta-blockers slow atrioventricular conduction and decrease heart rate. Concomitant use can increase the risk of bradycardia.

Other Precautions

In patients receiving thiazides, sensitivity reactions may occur with or without a history of allergy or bronchial asthma. The possible exacerbation or activation of systemic lupus erythematosus has been reported. The antihypertensive effects of thiazides may be enhanced in the postsympathectomy patient.

Carcinogenesis, Mutagenesis, Impairment of Fertility

Two long-term (maximum dosing duration of 18 or 24 months) rat studies and one long-term (maximum dosing duration of 18 months) mouse study, each employing dose levels as high as 300 mg/kg/day or 150 times the maximum recommended human antihypertensive dose*, did not indicate a carcinogenic potential of atenolol. A third (24 month) rat study, employing doses of 500 mg/kg/day and 1,500 mg/kg/day (250 and 750 times the maximum recommended human antihypertensive dose*) resulted in increased incidences of benign adrenal medullary tumors in males and females, mammary fibroadenomas in females, and anterior pituitary adenomas and thyroid parafollicular cell carcinomas in males. No evidence of a mutagenic potential of atenolol was uncovered in the dominant lethal test (mouse), in vivo cytogenetics test (Chinese hamster) or Ames test (S typhimurium).

Fertility of male or female rats (evaluated at dose levels as high as 200 mg/kg/day or 100 times the maximum recommended human dose*) was unaffected by atenolol administration.

*Based on the maximum dose of 100 mg/day in a 50 kg patient.

Animal Toxicology

Six month oral administration studies were conducted in rats and dogs using TENORETIC doses up to 12.5 mg/kg/day (atenolol/chlorthalidone 10/2.5 mg/kg/day -- approximately five times the maximum recommended human antihypertensive dose*). There were no functional or morphological abnormalities resulting from dosing either compound alone or together other than minor changes in heart rate, blood pressure and urine chemistry which were attributed to the known pharmacologic properties of atenolol and/or chlorthalidone.

Chronic studies of atenolol performed in animals have revealed the occurrence of vacuolation of epithelial cells of Brunner's glands in the duodenum of both male and female dogs at all tested dose levels (starting at 15 mg/kg/day or 7.5 times the maximum recommended human antihypertensive dose*) and increased incidence of atrial degeneration of hearts of male rats at 300 mg atenolol/kg/day but not 150 mg atenolol/kg/day (150 and 75 times the maximum recommended human antihypertensive dose,*respectively).

*Based on the maximum dose of 100 mg/day in a 50 kg patient.

Pregnancy

See WARNINGS - Pregnancy and Fetal Injury.

Nursing Mothers

Atenolol is excreted in human breast milk at a ratio of 1.5 to 6.8 when compared to the concentration in plasma. Caution should be exercised when atenolol is administered to a nursing woman. Clinically significant bradycardia has been reported in breastfed infants. Premature infants, or infants with impaired renal function, may be more likely to develop adverse effects.

Neonates born to mothers who are receiving atenolol at parturition or breastfeeding may be at risk for hypoglycemia and bradycardia. Caution should be exercised when TENORETIC is administered during pregnancy or to a woman who is breastfeeding. (See WARNINGS, Pregnancy and Fetal Injury.)

Pediatric Use

Safety and effectiveness in pediatric patients have not been established.

Geriatric Use

Clinical studies of TENORETIC did not include sufficient numbers of subjects aged 65 and over to determine whether they respond differently from younger subjects. Other reported clinical experience has not identified differences in responses between the elderly and younger patients. In general, dose selection for an elderly patient should be cautious, usually starting at the low end of the dosing range, reflecting the greater frequency of decreased hepatic, renal, or cardiac function, and concomitant disease or other drug therapy.

ADVERSE REACTIONS

TENORETIC is usually well tolerated in properly selected patients. Most adverse effects have been mild and transient. The adverse effects observed for TENORETIC are essentially the same as those seen with the individual components.

Atenolol

The frequency estimates in the following table were derived from controlled studies in which adverse reactions were either volunteered by the patient (US studies) or elicited, e.g., by checklist (foreign studies). The reported frequency of elicited adverse effects was higher for both atenolol and placebo-treated patients than when these reactions were volunteered. Where frequency of adverse effects for atenolol and placebo is similar, causal relationship to atenolol is uncertain.

 | Volunteered; (US Studies) |  | Total − Volunteered; and Elicited; (Foreign + US Studies)
 | Atenolol; (n = 164); % | Placebo; (n = 206); % | Atenolol; (n = 399); % | Placebo; (n = 407); %
CARDIOVASCULAR
Bradycardia | 3 | 0 | 3 | 0
Cold Extremities | 0 | 0.5 | 12 | 5
Postural Hypotension | 2 | 1 | 4 | 5
Leg Pain | 0 | 0.5 | 3 | 1
CENTRAL NERVOUS SYSTEM/; NEUROMUSCULAR
Dizziness | 4 | 1 | 13 | 6
Vertigo | 2 | 0.5 | 2 | 0.2
Light-Headedness | 1 | 0 | 3 | 0.7
Tiredness | 0.6 | 0.5 | 26 | 13
Fatigue | 3 | 1 | 6 | 5
Lethargy | 1 | 0 | 3 | 0.7
Drowsiness | 0.6 | 0 | 2 | 0.5
Depression | 0.6 | 0.5 | 12 | 9
Dreaming | 0 | 0 | 3 | 1
GASTROINTESTINAL
Diarrhea | 2 | 0 | 3 | 2
Nausea | 4 | 1 | 3 | 1
RESPIRATORY (see WARNINGS)
Wheeziness | 0 | 0 | 3 | 3
Dyspnea | 0.6 | 1 | 6 | 4

During postmarketing experience, the following have been reported in temporal relationship to the use of the drug: elevated liver enzymes and/or bilirubin, hallucinations, headache, impotence, Peyronie's disease, postural hypotension which may be associated with syncope, psoriasiform rash or exacerbation of psoriasis, psychoses, purpura, reversible alopecia, thrombocytopenia, visual disturbance, sick sinus syndrome, and dry mouth. TENORETIC, like other beta-blockers, has been associated with the development of antinuclear antibodies (ANA), lupus syndrome, and Raynaud’s phenomenon.

Chlorthalidone

Cardiovascular: orthostatic hypotension; Gastrointestinal: anorexia, gastric irritation, vomiting, cramping, constipation, jaundice (intrahepatic cholestatic jaundice), pancreatitis; CNS: vertigo, paresthesia, xanthopsia; Hematologic: leukopenia, agranulocytosis, thrombocytopenia, aplastic anemia; Hypersensitivity: purpura, photosensitivity, rash, urticaria, necrotizing angiitis (vasculitis) (cutaneous vasculitis), Lyell's syndrome (toxic epidermal necrolysis); Miscellaneous: hyperglycemia, glycosuria, hyperuricemia, muscle spasm, weakness, restlessness. Clinical trials of TENORETIC conducted in the United States (89 patients treated with TENORETIC) revealed no new or unexpected adverse effects.

POTENTIAL ADVERSE EFFECTS

In addition, a variety of adverse effects not observed in clinical trials with atenolol but reported with other beta-adrenergic blocking agents should be considered potential adverse effects of atenolol. Nervous System: Reversible mental depression progressing to catatonia; an acute reversible syndrome characterized by disorientation for time and place, short-term memory loss, emotional lability, slightly clouded sensorium, decreased performance on neuropsychometrics; Cardiovascular: Intensification of AV block (see CONTRAINDICATIONS); Gastrointestinal: Mesenteric arterial thrombosis, ischemic colitis; Hematologic: Agranulocytosis; Allergic: Erythematous rash, fever combined with aching and sore throat, laryngospasm and respiratory distress.

Miscellaneous

There have been reports of skin rashes and/or dry eyes associated with the use of beta-adrenergic blocking drugs. The reported incidence is small, and, in most cases, the symptoms have cleared when treatment was withdrawn. Discontinuance of the drug should be considered if any such reaction is not otherwise explicable. Patients should be closely monitored following cessation of therapy. (See DOSAGE AND ADMINISTRATION.)

The oculomucocutaneous syndrome associated with the beta-blocker practolol has not been reported with atenolol (TENORMIN). Furthermore, a number of patients who had previously demonstrated established practolol reactions were transferred to atenolol (TENORMIN) therapy with subsequent resolution or quiescence of the reaction.

To report SUSPECTED ADVERSE REACTIONS, contact TWi Pharmaceuticals, Inc. at 1-844-518-2989 or FDA at 1-800-FDA-1088 or www.fda.gov/medwatch for voluntary reporting of adverse reactions.

Clinical Laboratory Test Findings

Clinically important changes in standard laboratory parameters were rarely associated with the administration of TENORETIC. The changes in laboratory parameters were not progressive and usually were not associated with clinical manifestations. The most common changes were increases in uric acid and decreases in serum potassium.

OVERDOSAGE

No specific information is available with regard to overdosage and TENORETIC in humans. Treatment should be symptomatic and supportive and directed to the removal of any unabsorbed drug by induced emesis, or administration of activated charcoal. Atenolol can be removed from the general circulation by hemodialysis. Further consideration should be given to dehydration, electrolyte imbalance and hypotension by established procedures.

Atenolol

Overdosage with atenolol has been reported with patients surviving acute doses as high as 5 g. One death was reported in a man who may have taken as much as 10 g acutely.

The predominant symptoms reported following atenolol overdose are lethargy, disorder of respiratory drive, wheezing, sinus pause, and bradycardia. Additionally, common effects associated with overdosage of any beta-adrenergic blocking agent are congestive heart failure, hypotension, bronchospasm, and/or hypoglycemia. Other treatment modalities should be employed at the physician's discretion and may include:

BRADYCARDIA: Atropine 1 mg to 2 mg intravenously. If there is no response to vagal blockade, give isoproterenol cautiously. In refractory cases, a transvenous cardiac pacemaker may be indicated. Glucagon in a 10 mg intravenous bolus has been reported to be useful. If required, this may be repeated or followed by an intravenous infusion of glucagon 1 mg/h to 10 mg/h depending on response.

HEART BLOCK (SECOND OR THIRD DEGREE): Isoproterenol or transvenous pacemaker.

CONGESTIVE HEART FAILURE: Digitalize the patient and administer a diuretic. Glucagon has been reported to be useful.

HYPOTENSION: Vasopressors such as dopamine or norepinephrine (levarterenol). Monitor blood pressure continuously.

BRONCHOSPASM: A beta2-stimulant such as isoproterenol or terbutaline and/or aminophylline.

HYPOGLYCEMIA: Intravenous glucose.

ELECTROLYTE DISTURBANCE: Monitor electrolyte levels and renal function. Institute measures to maintain hydration and electrolytes.

Based on the severity of symptoms, management may require intensive support care and facilities for applying cardiac and respiratory support.

Chlorthalidone

Symptoms of chlorthalidone overdose include nausea, weakness, dizziness and disturbances of electrolyte balance.

DOSAGE AND ADMINISTRATION

DOSAGE MUST BE INDIVIDUALIZED. (See INDICATIONS AND USAGE.)

Chlorthalidone is usually given at a dose of 25 mg daily; the usual initial dose of atenolol is 50 mg daily. Therefore, the initial dose should be one TENORETIC 50 tablet given once a day. If an optimal response is not achieved, the dosage should be increased to one TENORETIC 100 tablet given once a day.

When necessary, another antihypertensive agent may be added gradually beginning with 50 percent of the usual recommended starting dose to avoid an excessive fall in blood pressure.

Since atenolol is excreted via the kidneys, dosage should be adjusted in cases of severe impairment of renal function. No significant accumulation of atenolol occurs until creatinine clearance falls below 35 mL/min/1.73m^2 (normal range is 100 mL/min/1.73m^2 to 150 mL/min/1.73m^2); therefore, the following maximum dosages are recommended for patients with renal impairment.

Creatinine Clearance; (mL/min/1.73m^2) | Atenolol; Elimination Half-Life; (hrs) | Maximum Dosage
15-35 | 16-27 | 50 mg daily
<15 | >27 | 50 mg every other day

HOW SUPPLIED

TENORETIC 50 Tablets (atenolol 50 mg and chlorthalidone 25 mg), are white, round, biconvex, uncoated tablets with TENORETIC on one side and 115 on the other side, bisected, supplied in bottles of 90 tablets (NDC 24979-256-07).

TENORETIC 100 Tablets (atenolol 100 mg and chlorthalidone 25 mg), are white, round, biconvex, uncoated tablets with TENORETIC on one side and 117 on the other side, supplied in bottles of 90 tablets (NDC 24979-257-07).

Store at controlled room temperature, 20°C to 25°C (68°F to 77°F) [see USP]. Dispense in well-closed, light-resistant containers.

TENORETIC is a trademark of TWi Pharmaceuticals, Inc.

Product of USA

Distributed by:
TWi Pharmaceuticals USA, Inc.
Paramus, NJ 07652

Revised: 01/2024

PKG03121

PACKAGE/LABEL PRINCIPAL DISPLAY PANEL – 50 mg

NDC 24979-256-07

Rx Only

Tenoretic® 50
(atenolol and chlorthalidone)

Each tablet contains:
50 mg atenolol and
25 mg chlorthalidone

90 tablets

PACKAGE/LABEL PRINCIPAL DISPLAY PANEL – 100 mg

NDC 24979-257-07

Rx Only

Tenoretic® 100
(atenolol and chlorthalidone)

Each tablet contains:
100 mg atenolol and
25 mg chlorthalidone

90 tablets